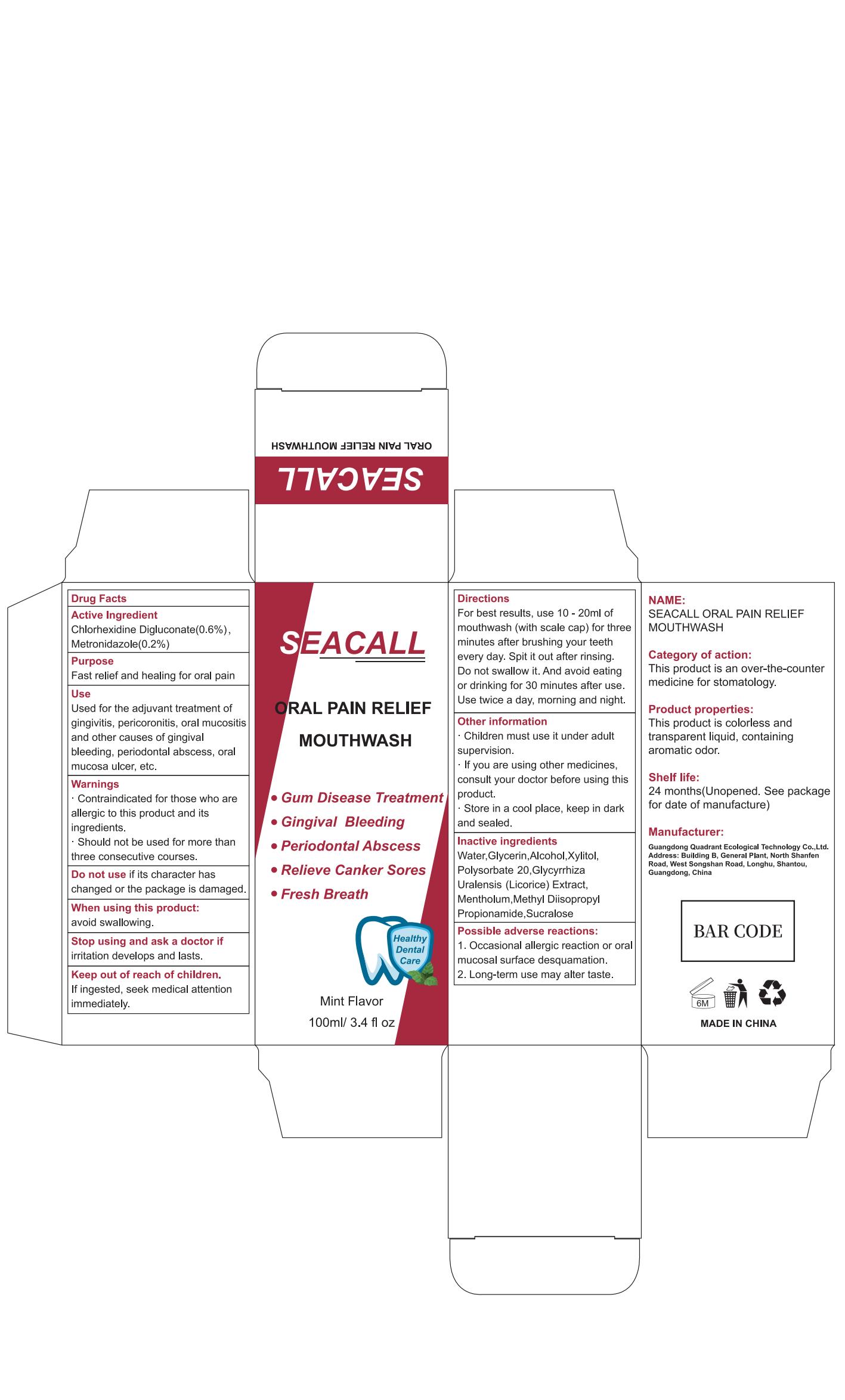 DRUG LABEL: SEACALL Mouthwash
NDC: 76986-005 | Form: LIQUID
Manufacturer: Guangdong Quadrant Ecological Technology Co., Ltd.
Category: otc | Type: HUMAN OTC DRUG LABEL
Date: 20250119

ACTIVE INGREDIENTS: METRONIDAZOLE 0.2 g/100 mL; CHLORHEXIDINE DIGLUCONATE 0.6 g/100 mL
INACTIVE INGREDIENTS: MENTHOL; XYLITOL; POLYSORBATE 20; ALCOHOL; GLYCYRRHIZA URALENSIS ROOT; METHYL DIISOPROPYL PROPIONAMIDE; SUCRALOSE; WATER; GLYCERIN

76986-005

Active Ingredient

Chlorhexidine Digluconate 0.6%

Metronidazole 0.2%

Purpose

Fast relief and healing for oral pain

Use

Used for the adjuvant treatment of gingivitis, pericoronitis, oral mucositis and other causes of gingival bleeding, periodontal abscess, oral mucosa ulcer, etc.

Warnings

· Contraindicated for those who are allergic to this product and its ingredients
· Should not be used for more than three consecutive courses.

Do not use

if its character has changed or the package is damaged.

When Using

avoid swallowing.

Stop Use

if irritation develops and lasts.

Ask Doctor

if irritation develops and lasts.

Keep Oot Of Reach Of Children

If ingested, seek medical attention immediately.

Directions

For best results, use 10 - 20ml of mouthwash (with scale cap) for three minutes after brushing your teeth every day. Spit it out after rinsing. Do not swallow it. And avoid eating or drinking for 30 minutes after use. Use twice a day, morning and night.

Other information

· Children must use it under adult supervision.
· If you are using other medicines, consult your doctor before using this product.
· Store in a cool place, keep in dark and sealed.

Inactive ingredients

Water,Glycerin,Alcohol,Xylitol,Polysorbate 20,Glycyrrhiza Uralensis (Licorice) Extract, Mentholum,Methyl Diisopropyl Propionamide,Sucralose